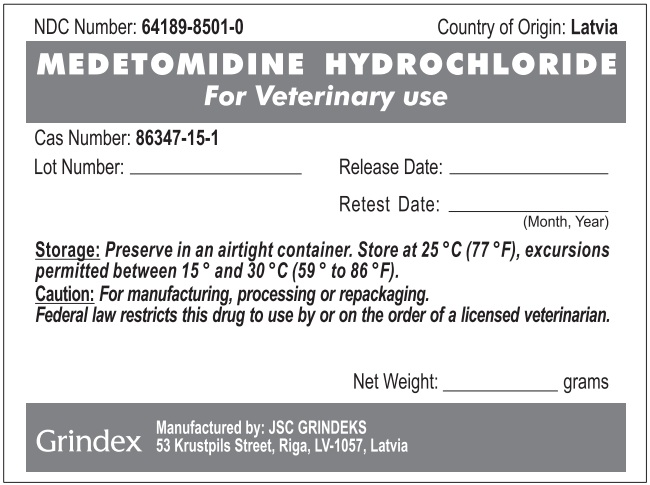 DRUG LABEL: Medetomidine Hydrochloride
NDC: 64189-8501 | Form: POWDER
Manufacturer: GRINDEKS Joint Stock Company
Category: other | Type: BULK INGREDIENT - ANIMAL DRUG
Date: 20251216

ACTIVE INGREDIENTS: MEDETOMIDINE HYDROCHLORIDE 1 g/1 g

Medetomidine Hydrochloride

WARNINGS AND PRECAUTIONS

Caution: For manufacturing, processing, or repackaging.

Federal Law restricts this drug to use by or on the order of a licensed veterinarian.

STORAGE AND HANDLING

Storage: Preserve in an airtight container. Store at 25°C (77°F), excursions permitted between 15° and 30°C (59° to 86°F).

PACKAGE LABEL

NDC Number: 64189-8501-0 Country of Origin: Latvia

MEDETOMIDINE HYDROCHLORIDE

For Veterinary Use

Cas Number: 86347-15-1

Lot Number:_______________ Release Date:____________

Retest Date:_____________ (Month, Year)

Storage: Preserve in an airtight container. Store at 25°C (77°F), excursions permitted between 15° and 30°C (59° to 86°F).

Caution: For manufacturing, processing, or repackaging. Federal law restricts this drug to use by or on the order of a licensed veterinarian.

Net Weight:_____________grams

Grindex

Manufactured by: JSC GRINDEKS

53 Krustpils Street, Riga, LV-1057, Latvia